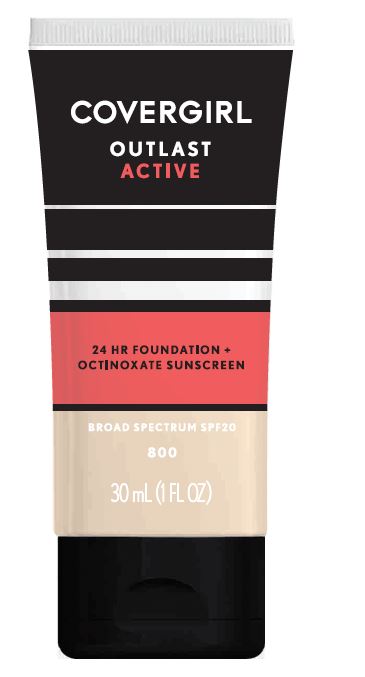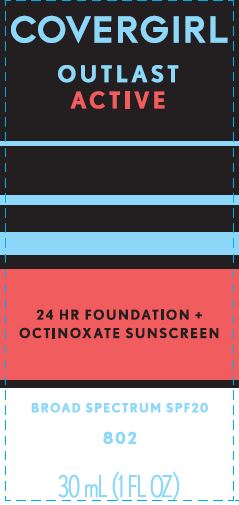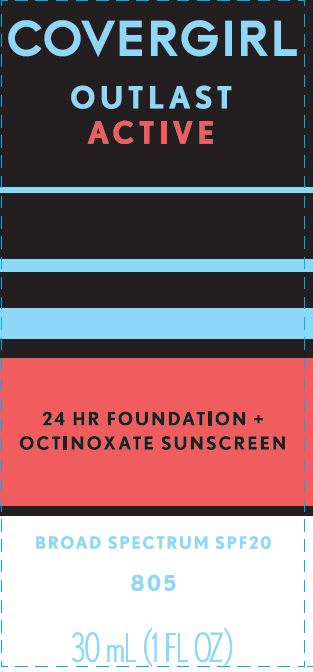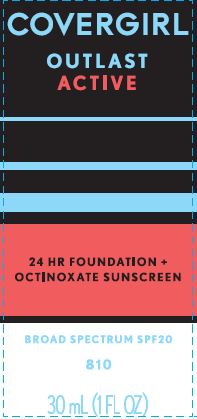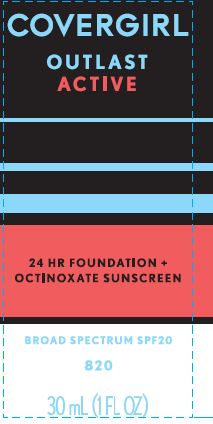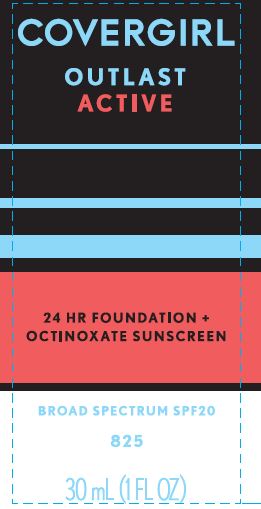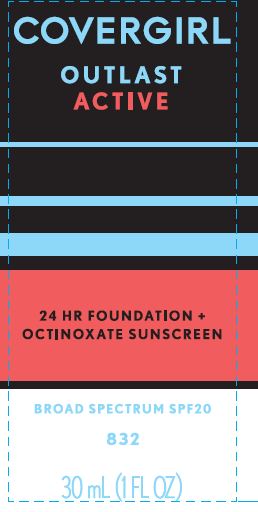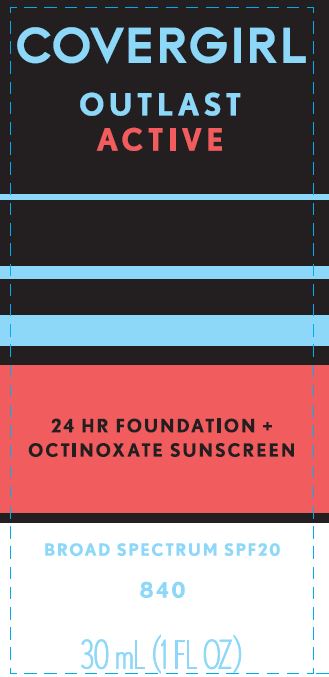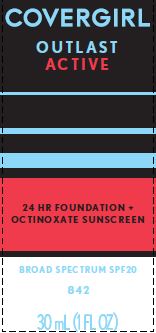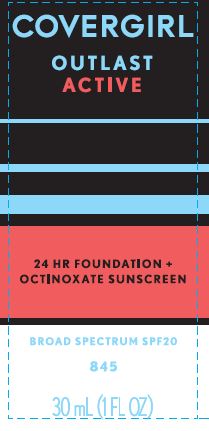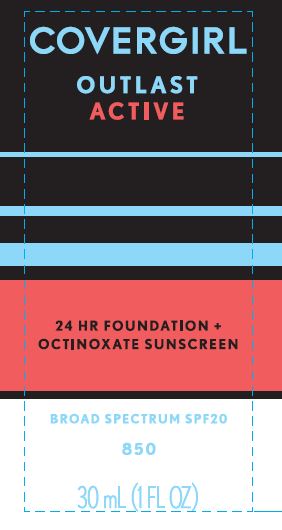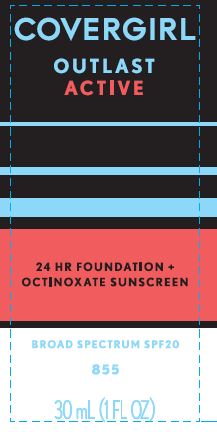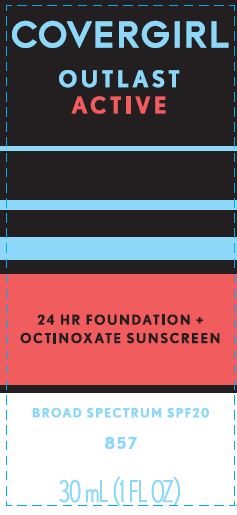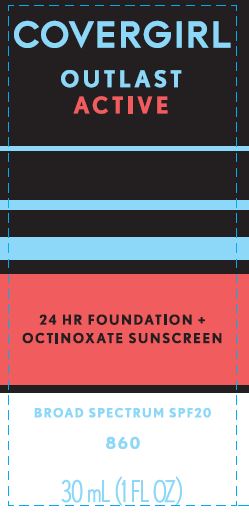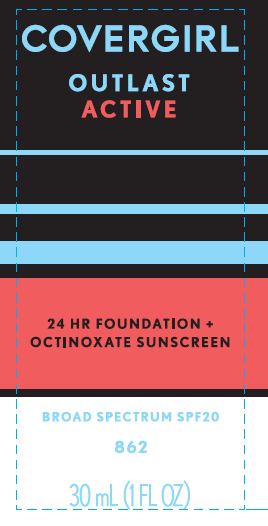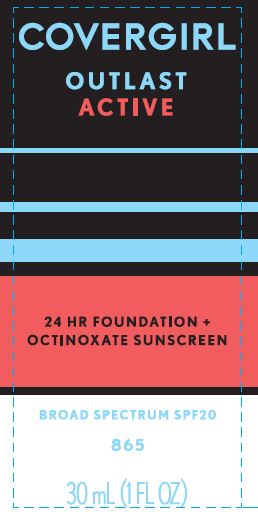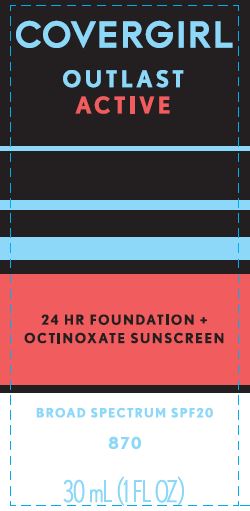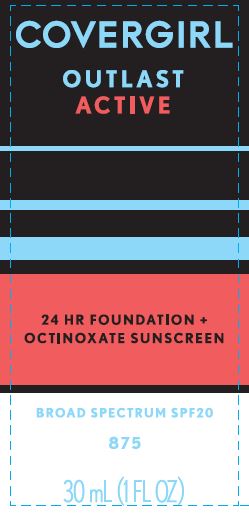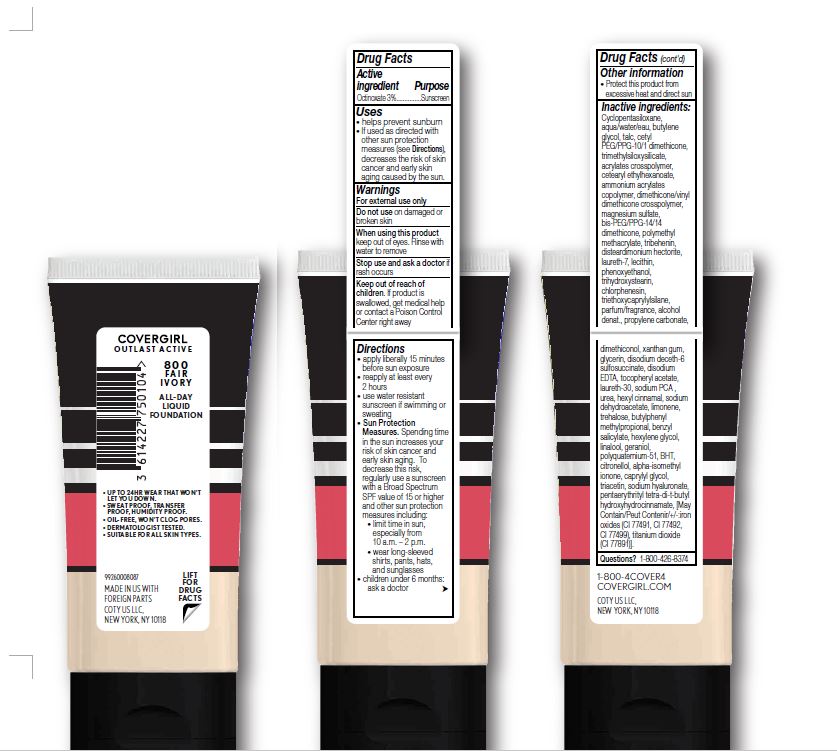 DRUG LABEL: Covergirl Outlast Active Foundation SPF 20
NDC: 22700-156 | Form: LIQUID
Manufacturer: Noxell Corporation
Category: otc | Type: HUMAN OTC DRUG LABEL
Date: 20230124

ACTIVE INGREDIENTS: OCTINOXATE 3 g/100 mL
INACTIVE INGREDIENTS: CETYL PEG/PPG-10/1 DIMETHICONE (HLB 2); BIS-PEG/PPG-14/14 DIMETHICONE; DISTEARDIMONIUM HECTORITE; TRIETHOXYCAPRYLYLSILANE; PHENOXYETHANOL; TALC; TRIMETHYLSILOXYSILICATE (M/Q 0.6-0.8); MAGNESIUM SULFATE, UNSPECIFIED FORM; CHLORPHENESIN; PROPYLENE CARBONATE; DIMETHICONOL (100000 CST); GLYCERIN; LIMONENE, (+)-; BUTYLPHENYL METHYLPROPIONAL; TRIBEHENIN; BUTYLENE GLYCOL; CETEARYL ETHYLHEXANOATE; CAPRYLYL GLYCOL; DIMETHICONE/VINYL DIMETHICONE CROSSPOLYMER (HARD PARTICLE); XANTHAN GUM; SODIUM DEHYDROACETATE; TITANIUM DIOXIDE; WATER; LAURETH-7; BENZYL SALICYLATE; TRIACETIN

COVERGIRL OUTLAST ACTIVE FOUNDATION SPF 20

Active ingredent

Octinoxate 3%

Purpose

Sunscreen

Uses

- helps prevent sunburn
- if used as directed with other sun protection measures (see Directions), decreases the risk of skin cancer and early skin skin aging caused by the sun.

Warnings

For external use only

Do not use

on damaged or broken skin

When using this product

keep out of eyes. Rinse with water to remove.

Stop use and ask a doctor

if rash occurs.

Keep out of reach of children.

If product is swallowed, get medical help or contact a Poison Control Center right away.

Directions

- apply liberally 15 minutes before sun exposure
- reapply at least every 2 hours
- use a water resistant sunscreen if swimming or sweating
- Sun Protection Measures. Spending time in the sun increases your risk of skin cancer and early skin aging. To decrease this risk, regularly use a sunscreen with a Broad Spectrum SPF value of 15 or higher and other sun protection measures including: limit time in the sun, especially from 10 a.m.-2 p.m., wear long-sleeved shirts, pants, hats and sunglasses
- children under 6 months: ask a doctor

Other information

- Protect this product from excessive heat and direct sun

Inactive ingredients

Cyclopentasiloxane, Aqua/Water/Eau, Butylene Glycol, Talc, Cetyl PEG/PPG-10/1 Dimethicone,

Trimethylsiloxysilicate, Acrylates Crosspolymer, Cetearyl Ethylhexanoate, Ammonium Acrylates Copolymer, Dimethicone/Vinyl Dimethicone Crosspolymer, Magnesium Sulfate, Bis-PEG/PPG-14/14 Dimethicone, Polymethyl Methacrylate, Tribehenin, Disteardimonium Hectorite, Laureth-7, Lecithin, Phenoxyethanol, Trihydroxystearin, Chlorphenesin, Triethoxycaprylylsilane, Parfum/Fragrance, Alcohol Denat., Propylene Carbonate, Dimethiconol, Xanthan Gum, Glycerin, Disodium Deceth-6 Sulfosuccinate, Disodium EDTA, Tocopheryl Acetate, Laureth-30, Sodium PCA , Urea, Hexyl Cinnamal, Sodium Dehydroacetate, Limonene, Trehalose, Butylphenyl Methylpropional, Benzyl Salicylate, Hexylene Glycol, Linalool, Geraniol, Polyquaternium-51, BHT, Citronellol, Alpha-Isomethyl Ionone, Caprylyl Glycol, Triacetin, Sodium Hyaluronate, Pentaerythrityl Tetra-di-t-butyl Hydroxyhydrocinnamate, [May Contain/Peut Contenir/+/-:Iron Oxides (CI 77491, CI 77492, CI 77499), Titanium Dioxide (CI 77891)].

Questions?

1-800-426-8374

PACKAGE LABEL

COVERGIRL

OUTLAST ACTIVE

24 HR FOUNDATION +

OCTINOXATE SUNSCREEN

BROAD SPECTRUM SPF20

30 mL (1 FL OZ)